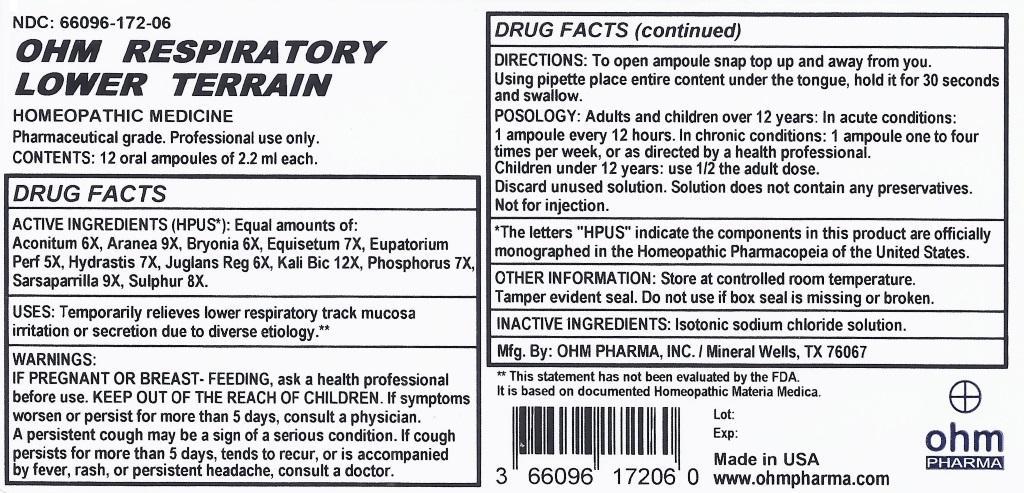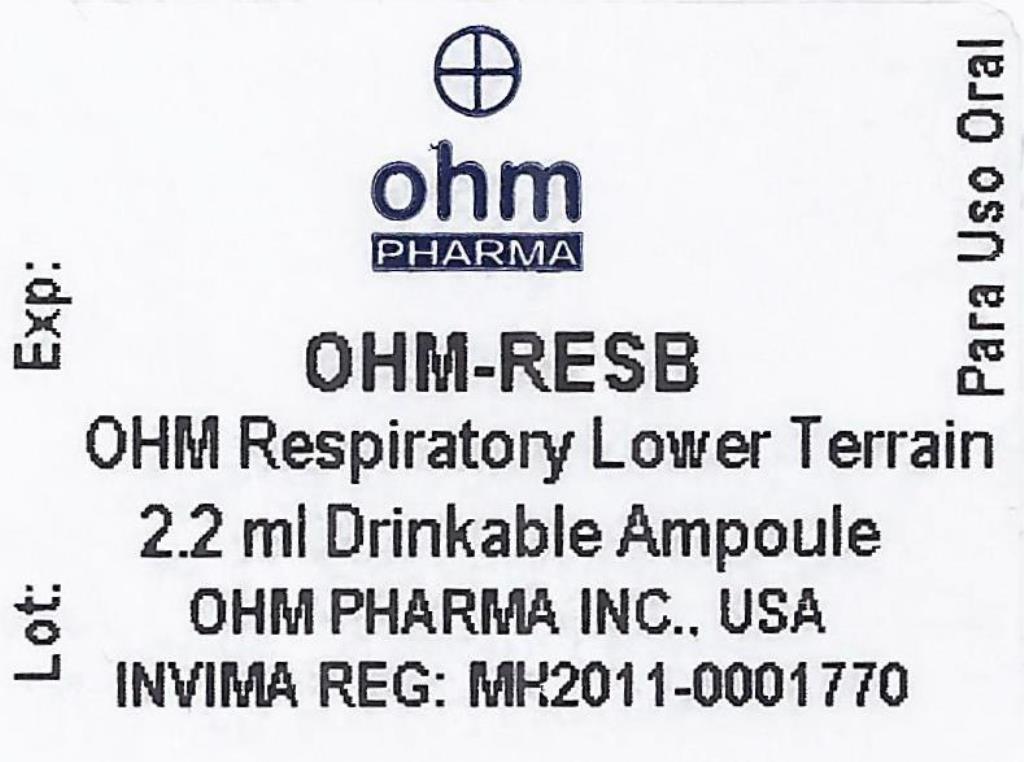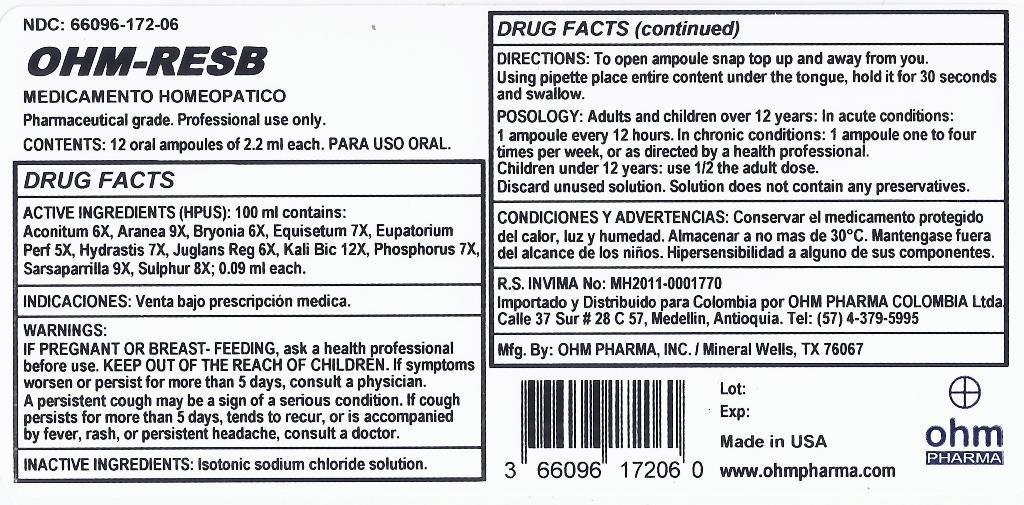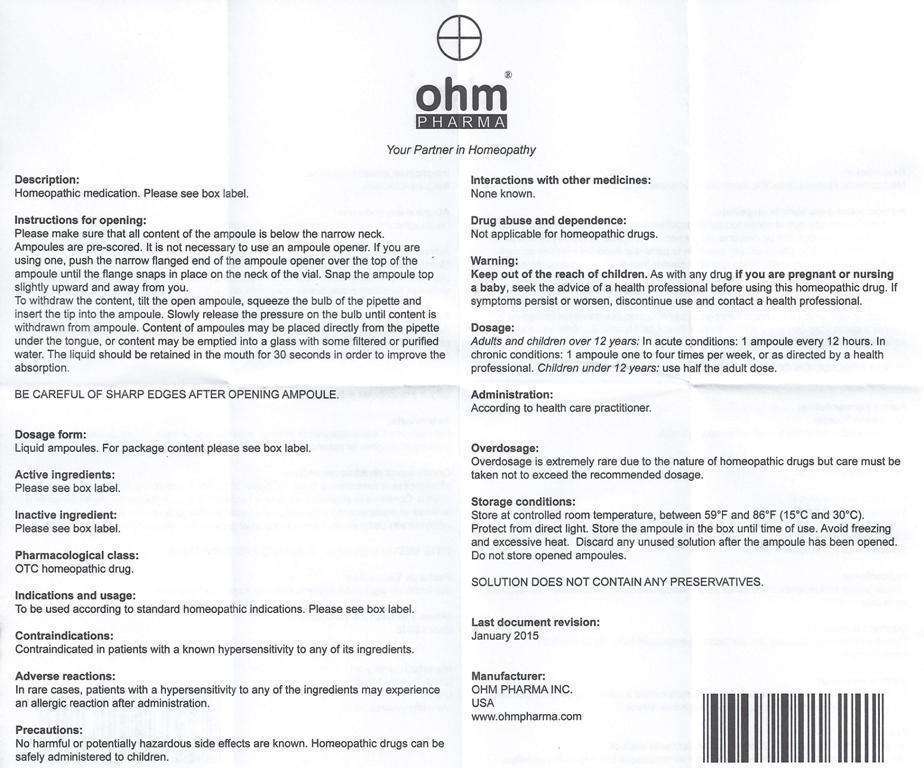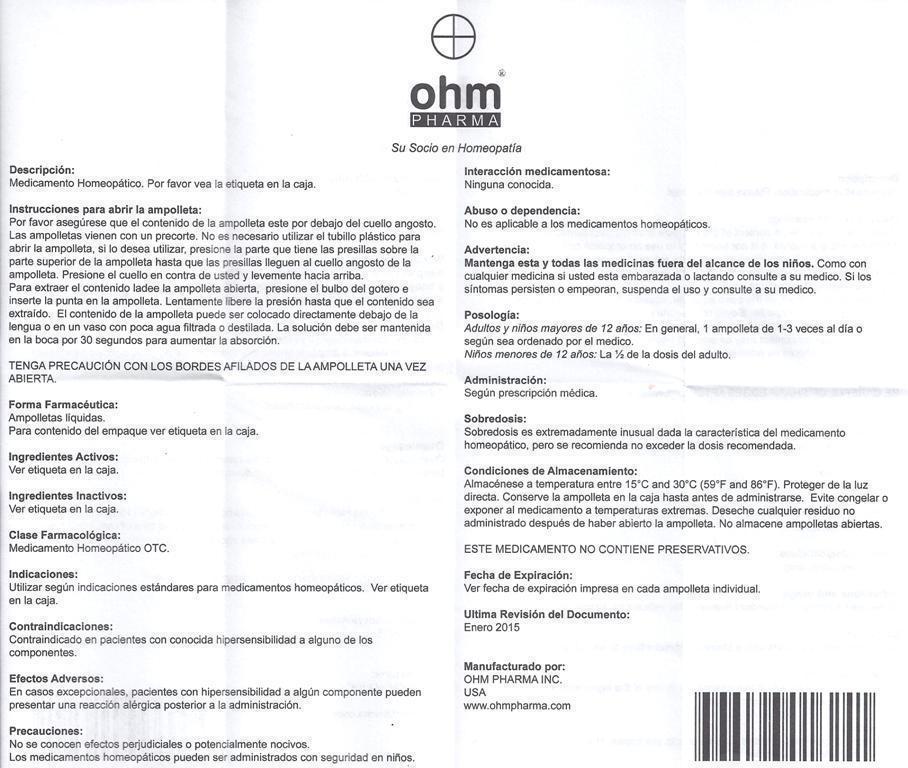 DRUG LABEL: OHM RESPIRATORY LOWER TERRAIN
NDC: 66096-172 | Form: LIQUID
Manufacturer: OHM PHARMA INC.
Category: homeopathic | Type: HUMAN OTC DRUG LABEL
Date: 20160112

ACTIVE INGREDIENTS: ACONITUM NAPELLUS 6 [hp_X]/1 mL; ARANEUS DIADEMATUS 9 [hp_X]/1 mL; BRYONIA ALBA ROOT 6 [hp_X]/1 mL; EQUISETUM HYEMALE 7 [hp_X]/1 mL; EUPATORIUM PERFOLIATUM FLOWERING TOP 5 [hp_X]/1 mL; GOLDENSEAL 7 [hp_X]/1 mL; JUGLANS REGIA LEAF 6 [hp_X]/1 mL; POTASSIUM DICHROMATE 12 [hp_X]/1 mL; PHOSPHORUS 7 [hp_X]/1 mL; SMILAX REGELII ROOT 9 [hp_X]/1 mL; SULFUR 8 [hp_X]/1 mL
INACTIVE INGREDIENTS: SODIUM CHLORIDE

OHM RESPIRATORY LOWER TERRAIN

ACTIVE INGREDIENT

ACTIVE INGREDIENTS (HPUS*): Equal amounts of: Aconitum 6X, Aranea 9X, Bryonia 6X, Equisetum 7X, Eupatorium Perf 5X, Hydrastis7X, Juglans Reg 6X, Kali Bic 12X, Phosphorus 7X, Sarsaparrilla 9X, Sulphur 8X.

ACTIVE INGREDIENT

*The letters "HPUS" indicate the components in this product are officially monographed in the Homeopathic Pharmacopeia of the United States.

INDICATIONS AND USAGE

USES: Temporarily relieves lower respiratory track mucosa irritation or secretion due to diverse etiology.**

**This statement has not been evaluated by the FDA.
It is based on documented Homeopathic Materia Medica.

WARNINGS:

IF PREGNANT OR BREAST-FEEDING, ask a health professional before use. If symptoms worsen or persist for more than 5 days, consult a physician. A persistent cough may be a sign of a serious condition. If cough persists for more than 5 days, tends to recur, or is accompanied by fever, rash, or persistent headache, consult a doctor.

KEEP OUT OF THE REACH OF CHILDREN.

DOSAGE AND ADMINISTRATION

DIRECTIONS: To open ampoule snap top up and away from you. Using pipette place entire content under the tongue, hold it for 30 seconds and swallow.

POSOLOGY: Adults and children over 12 years: In acute conditions: 1 ampoule every 12 hours. In chronic conditions: 1 ampoule one to four times per week, or as directed by a health professional.

Children under 12 years use 1/2 the adult dose.

Discard unused solution. Solution does not contain any preservatives.

Not for injection.

OTHER INFORMATION: Store at controlled room temperature. Tamper evident seal. Do not use if box seal is missing or broken.

INACTIVE INGREDIENTS: Isotonic sodium chloride solution.

QUESTIONS

Mfg. By: OHM PHARMA, INC. / Mineral Wells, TX 76067

Made in USA

www.ohmpharma.com

PURPOSE

Acute or chronic functional ailments of the kidneys and/or urinary track relief

PACKAGE LABEL

NDC: 66096-172-06

OHM RESPIRATORY LOWER TERRAIN

HOMEOPATHIC MEDICINE

Pharmaceutical Grade. Professional use only.

CONTENTS: 12 oral ampoules of 2.2 ml each.